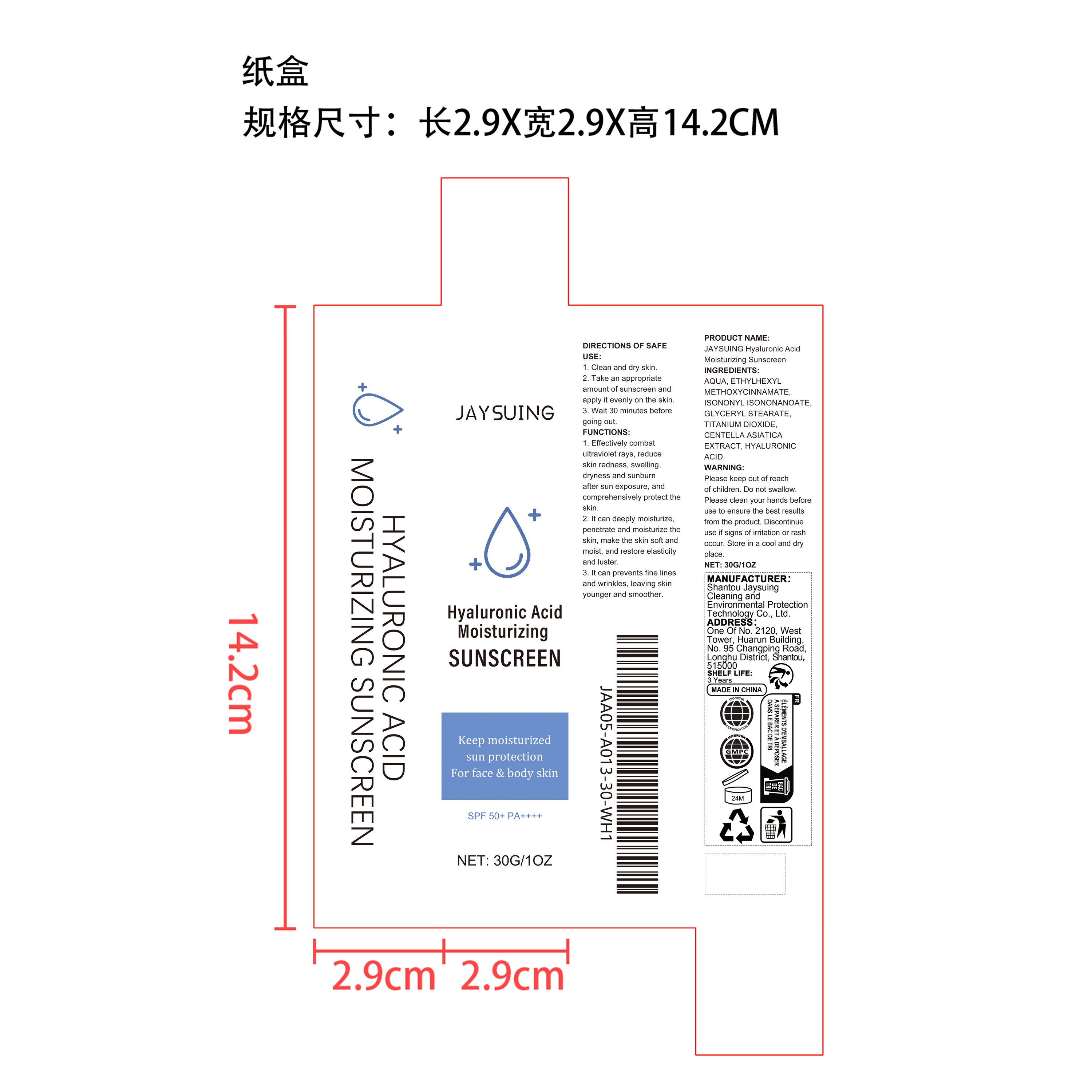 DRUG LABEL: JAYSUING Hyaluronic Acid Moisturizing Sunscreen
NDC: 85060-013 | Form: LIQUID
Manufacturer: Shantou Jaysuing Cleaning and Environmental Protection Technology Co., Ltd.
Category: otc | Type: HUMAN OTC DRUG LABEL
Date: 20260114

ACTIVE INGREDIENTS: CENTELLA ASIATICA LEAF 0.006 mg/30 mg
INACTIVE INGREDIENTS: HYALURONIC ACID 0.015 mg/30 mg; ISONONYL ISONONANOATE 1.2 mg/30 mg; TITANIUM DIOXIDE 0.3 mg/30 mg; ETHYLHEXYL METHOXYCINNAMATE 1.5 mg/30 mg; GLYCERYL STEARATE 0.45 mg/30 mg; AQUA 26.529 mg/30 mg

ACTIVE INGREDIENT

CENTELLA ASIATICA EXTRACT

PURPOSE

1. Effectively combat ultraviolet rays, reduce skin redness, swelling, dryness and sunburn after sun exposure, and comprehensively protect the skin.

2. It can deeply moisturize, penetrate and moisturize the skin, make the skin soft and moist, and restore elasticity and luster.

3. It can prevents fine lines and wrinkles, leaving skin younger and smoother.

WHEN USING

1. Clean and dry skin

2. Take an appropriate amount of sunscreen and apply it evenly on the skin

3. Wait 30 minutes before going out

WARNINGS

Please keep out of reach of children. Do not swallow.Please clean your hands before use to ensure the best results from the product. Discontinue use if signs of irritation or rash occur. Store in a cool and dry place.

DO NOT USE

Discontinue use if signs of irritation or rash occur.

STOP USE

Discontinue use if signs of irritation or rash occur.

KEEP OUT OF REACH OF CHILDREN

Please keep out of reach of children. Do not swallow.

STORAGE AND HANDLING

Store in a cool and dry place.

INACTIVE INGREDIENT

AQUA、ETHYLHEXYL METHOXYCINNAMATE、ISONONYL ISONONANOATE、GLYCERYL STEARATE、HYALURONIC ACID

DOSAGE AND ADMINISTRATION

1. Clean and dry skin

2. Take an appropriate amount of sunscreen and apply it evenly on the skin

3. Wait 30 minutes before going out

INDICATIONS AND USAGE

1. Clean and dry skin

2. Take an appropriate amount of sunscreen and apply it evenly on the skin

3. Wait 30 minutes before going out